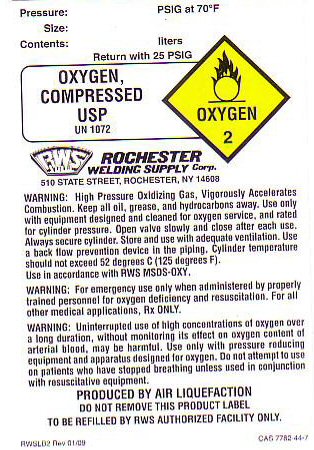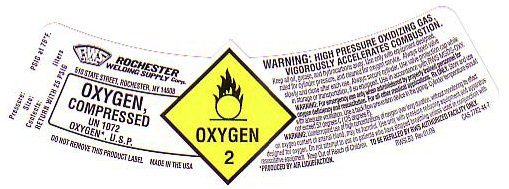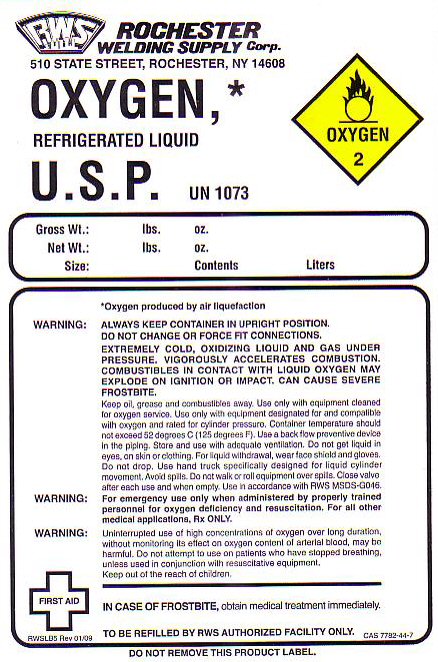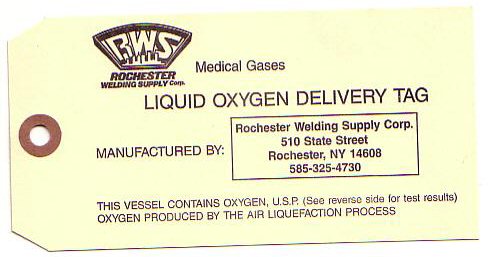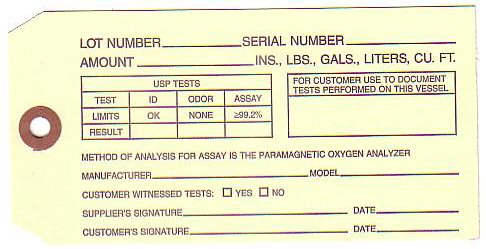 DRUG LABEL: OXYGEN
NDC: 53828-001 | Form: GAS
Manufacturer: Rochester Welding Supply Corp.
Category: prescription | Type: HUMAN PRESCRIPTION DRUG LABEL
Date: 20100101

ACTIVE INGREDIENTS: OXYGEN 99 L/100 L

OXYGEN COMPRESSED LABEL

OXYGEN COMPRESSED USP - OXYGEN-2

PRESSURE:_________ PSIG AT 70 F SIZE: ______________ CONTENTS____________LITERS RETURN WITH 25 PSIG. UN 1072

PRODUCED BY AIR LIQUEFACTION TO BE REFILLED BY RWS AUTHORIZED FACILITY ONLY CAS 7782-44-7 RWSLB2 REV 01/09

OXYGEN COMPRESSED LABEL

OXYGEN COMPRESSED USP - OXYGEN-2
PRESSURE:_________ PSIG AT 70 F SIZE: ______________ CONTENTS____________LITERS RETURN WITH 25 PSIG. UN 1072
PRODUCED BY AIR LIQUEFACTION TO BE REFILLED BY RWS AUTHORIZED FACILITY ONLY CAS 7782-44-7 RWSLB3 REV 01/09 MADE IN THE USA

REFRIGERATED LIQUID LABEL

OXYGEN REFRIGERATED LIQUID U.S.P. UN 1073 OXYGEN-2

GROSS WT:____ LBS. OZ. NET WT. _____________ LBS. OZ. SIZE______________ CONTENTS___________ LITERS

OXYGEN PRODUCED BY AIR LIQUEFACTION ALWAYS KEEP CONTAINER IN UPRIGHT POSITION. DO NOT CHANGE OR FORCE FIT CONNECTIONS. EXTREMELY COLD, OXIDIZING LIQUID AND GAS UNDER PRESSURE. VIGOROUSLY ACCELERATES COMBUSTION. COMBUSTIBLES IN CONTACT WITH LIQUID OXYGEN MAY EXPLODE ON IGNITION OR IMPACT. CAN CAUSE SEVERE FROSTBITE.

FOR LIQUID WITHDRAWAL WEAR FACE SHIELD AND GLOVES. DO NOT GET LIQUID IN EYES, ON SKIN OR CLOTHING. DO NOT DROP. USE HAND TRUCK SPECIFICALLY DESIGNED FOR LIQUID CYLINDER MOVEMENT. AVOID SPILLS. DO NOT WALK OR ROLL EQUIPMENT OVER SPILLS. USE IN ACCORDANCE WITH RWS MSDS-G046

IN CASE OF FROSTBITE OBTAIN MEDICAL TREATMENT IMMEDIATELY. CAS 7782-44-7 RWSLB5 REV 01/09 OXYGEN PRODUCED BY AIR LIQUEFACTION

OXYGEN CERTIFICATE OF ANALYSIS

LOT NUMBER____ SERIAL NUMBER________ AMOUNT_____________ INS. LBS GALS LITERS CU FT

USP TESTS

TEST ID ODOR ASSAY

LIMITS OK NONE GREATER THAN OR EQUAL TO 99.2%

RESULTS __ _____ _______

FOR CUSTOMER USE TO DOCUMENT TESTS PERFORMED ON THIS VESSEL

METHOD OF ANALYSIS IS THE PARAMAGNETIC OXYGEN ANALYZER

MANUFACTURER __________ MODEL ________ CUSTOMER WITNESSED TESTS YES__ MO___ SUPPLIERS SIGNATURE _____________ DATE____ CUSTOMER'S SIGNATURE___________ DATE___________

LIQUID OXYGEN DELIVERY TAG THIS VESSEL CONTAINS OXYGEN U.S.P. (SEE REVERSE SIDE FOR TEST RESULTS) OXYGEN PRODUCED BY THE AIR LIQUEFACTION PROCESS - MEDICAL GASES

MANUFACTURED BY ROCHESTER WELDING SUPPLY CORP 510 STATE STREET ROCHESTER, NY 14608 585-325-4730

PRODUCT WARNINGS AND PRECAUTIONS

KEEP ALL OIL, GREASE, AND HYDROCARBONS AWAY. USE ONLY WITH EQUIPMENT DESIGNED AND CLEANED FOR OXYGEN SERVICE AND RATED FOR CYLINDER PRESSURE. OPEN VALVE SLOWLY AND CLOSE AFTER EACH USE. ALWAYS SECURE CYLINDER. STORE AND USE WITH ADEQUATE VENTILATION. USE A BACK FLOW PREVENTATIVE DEVICE IN THE PIPING. CYLINDER TEMPERATURE SHOULD NOT EXCEED 52 DEGREES C (125 DEGREES F) USE IN ACCORDANCE WITH RWS MSDS-OXY.

WARNING: FOR EMERGENCY USE ONLY WHEN ADMINISTERED BY PROPERLY TRAINED PERSONNEL FOR OXYGEN DEFICIENCY AND RESUSCITATION. FOR ALL OTHER MEDICAL APPLICATIONS Rx ONLY.

WARNING: UNINTERRUPTED USE OF HIGH CONCENTRATIONS OF OXYGEN OVER A LONG DURATION, WITHOUT MONITORING ITS EFFECT ON OXYGEN CONTENT OF ARTERIAL BLOOD, MAY BE HARMFUL. USE ONLY WITH PRESSURE REDUCING EQUIPMENT AND APPARATUS DESIGNED FOR OXYGEN. DO NOT ATTEMPT TO USE ON PATIENTS WHO HAVE STOPPED BREATHING UNLESS USED IN CONJUNCTION WITH RESUSCITATIVE EQUIPMENT.

DO NOT REMOVE THIS PRODUCT LABEL.